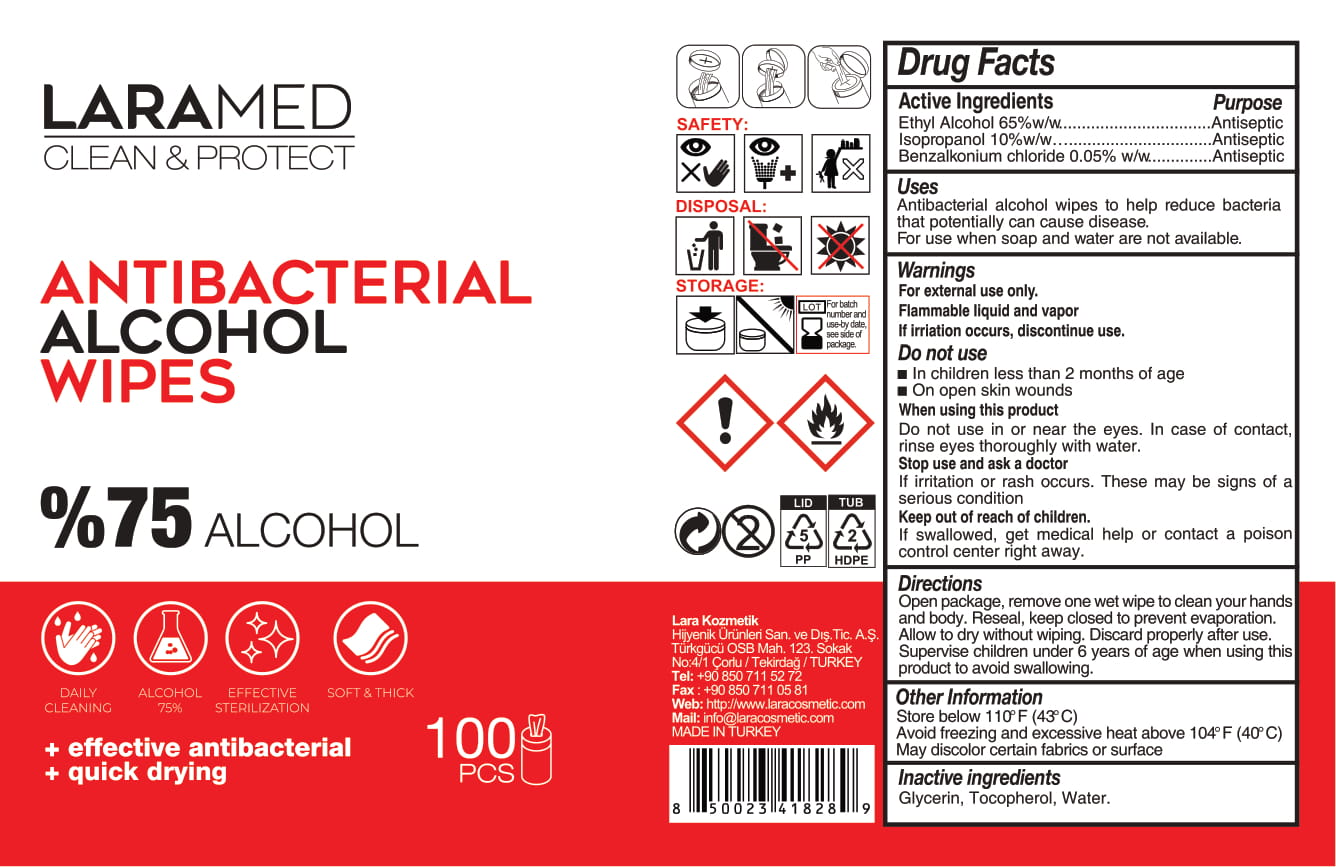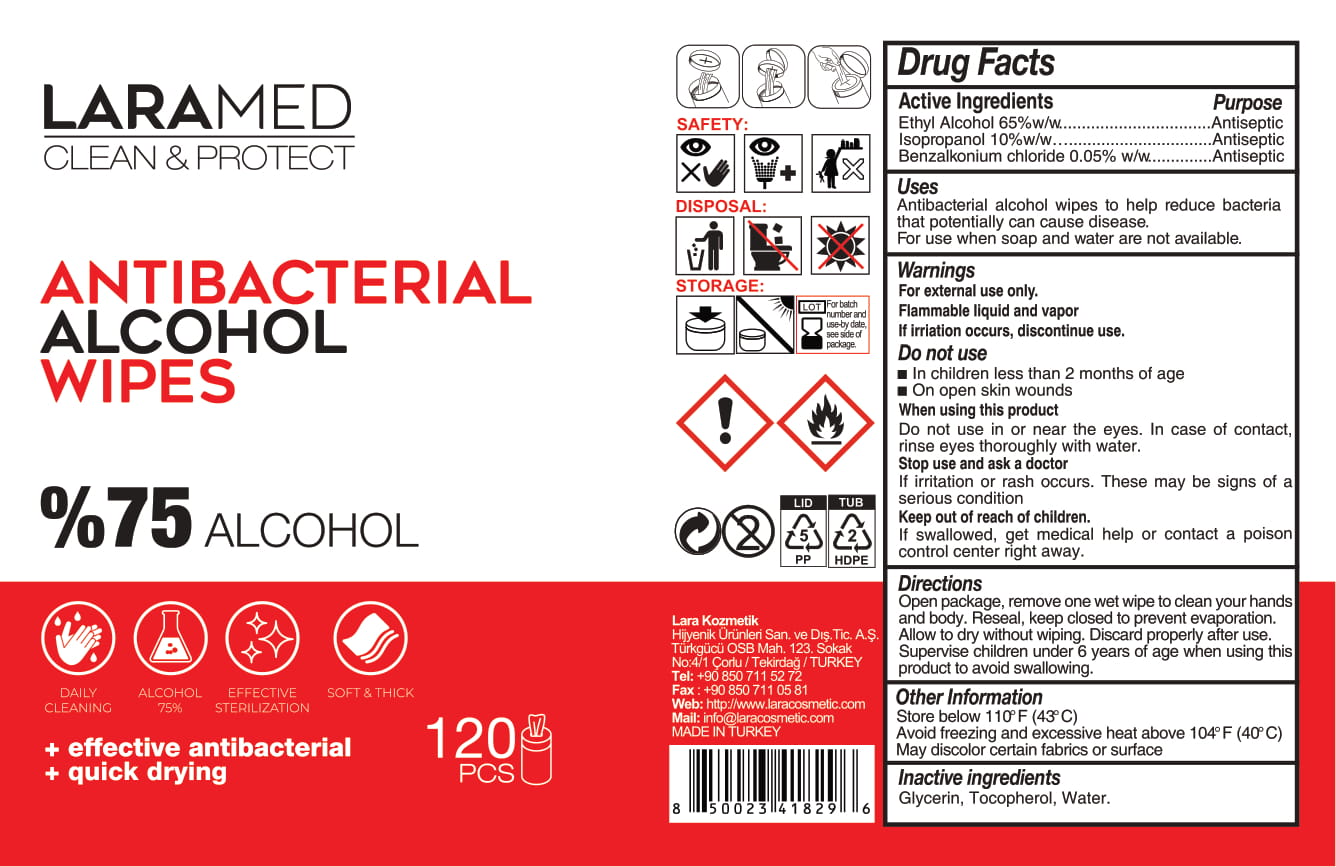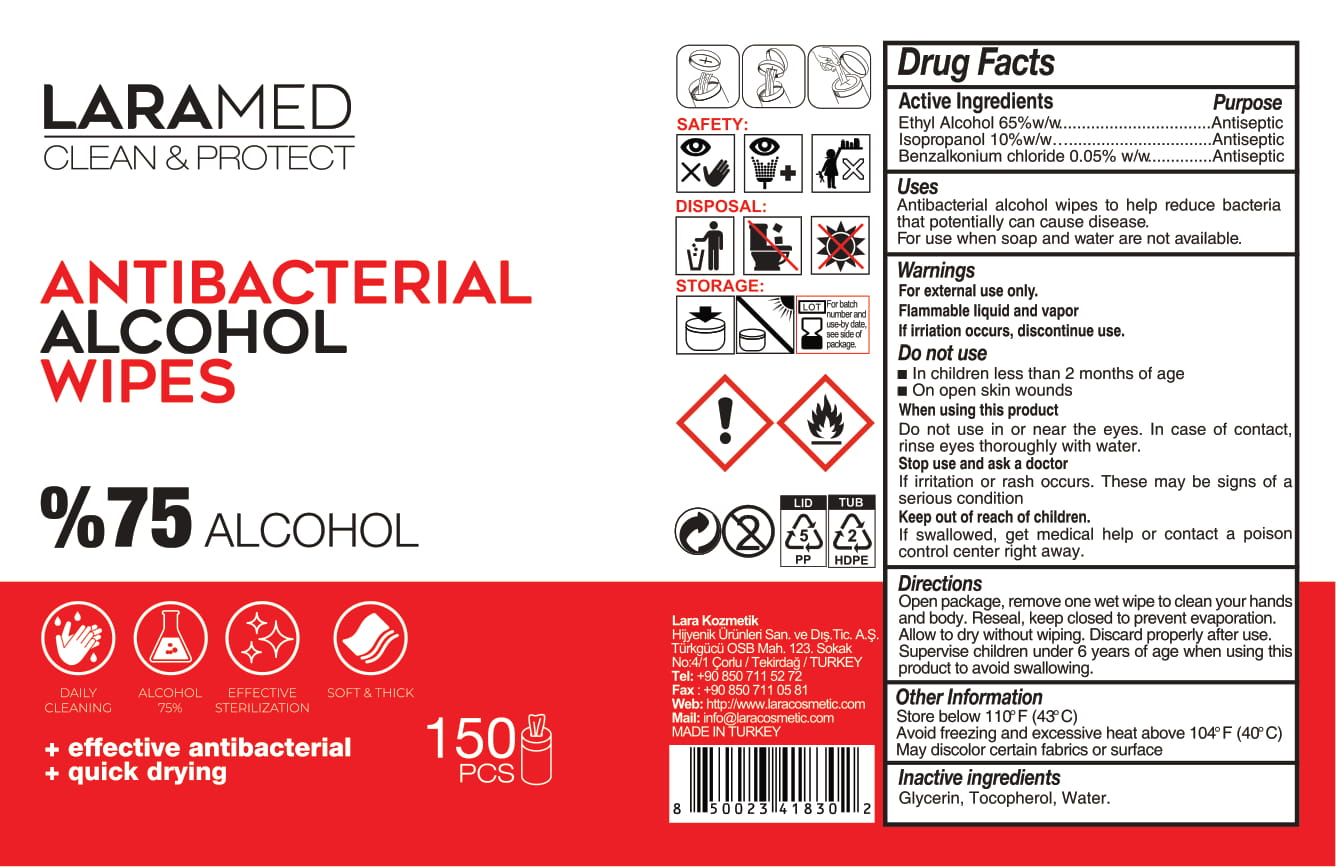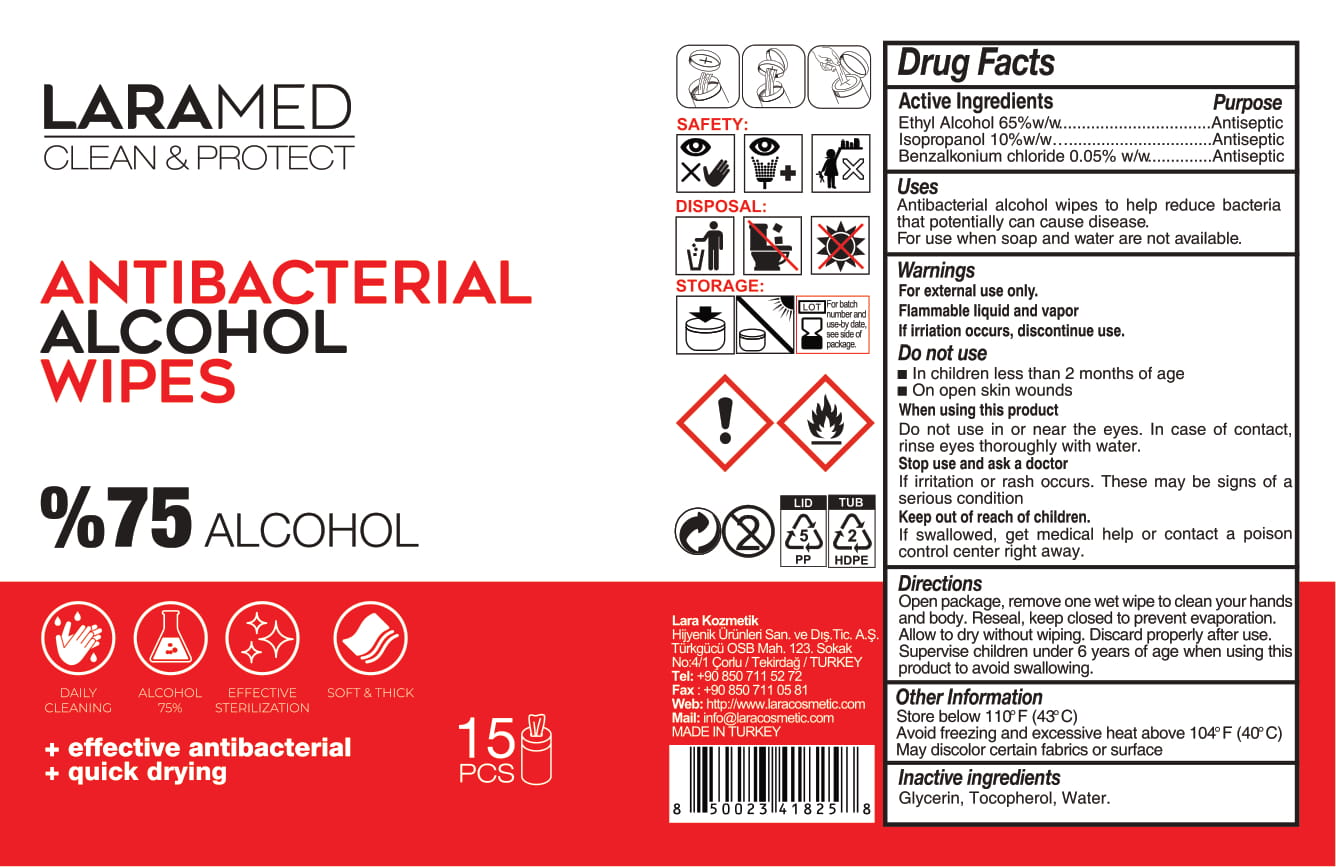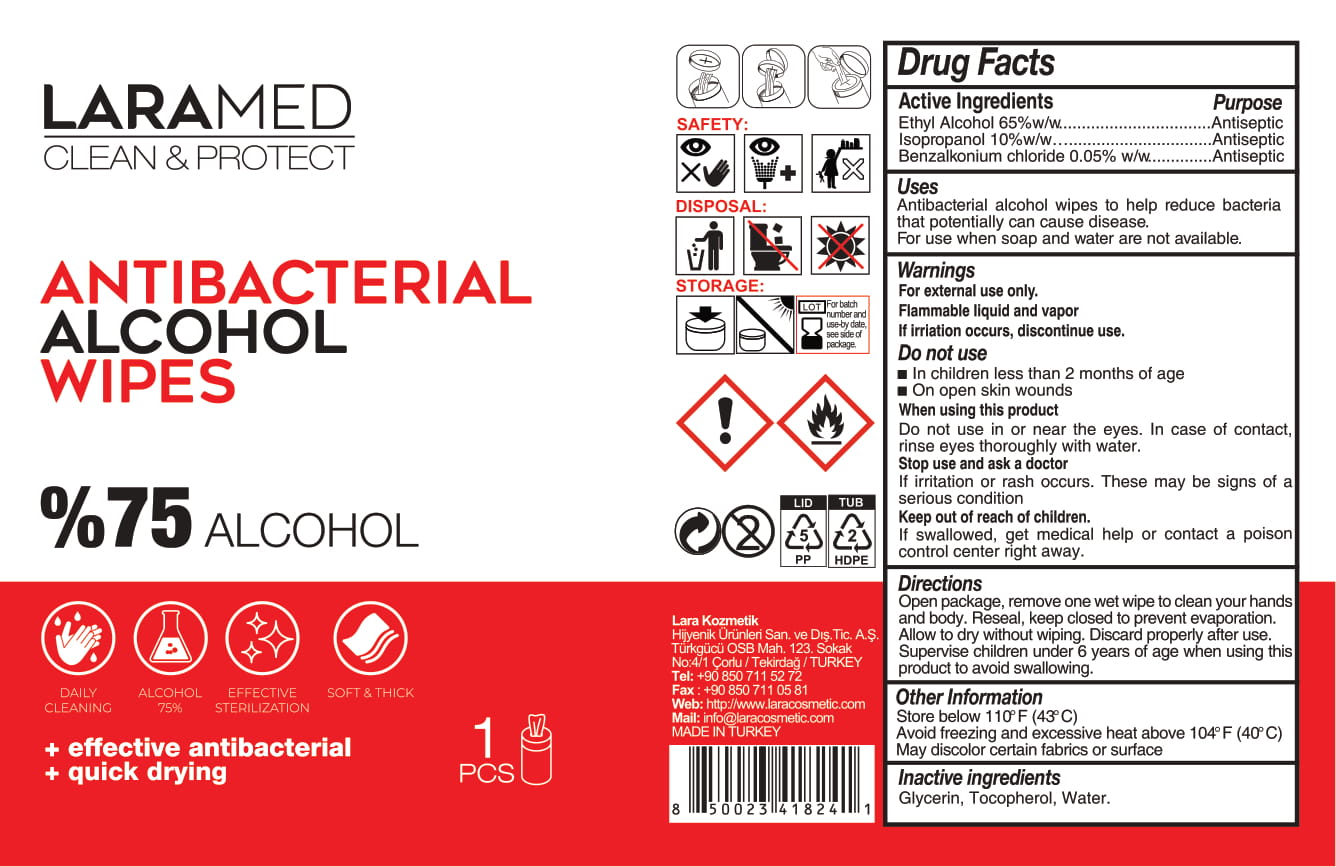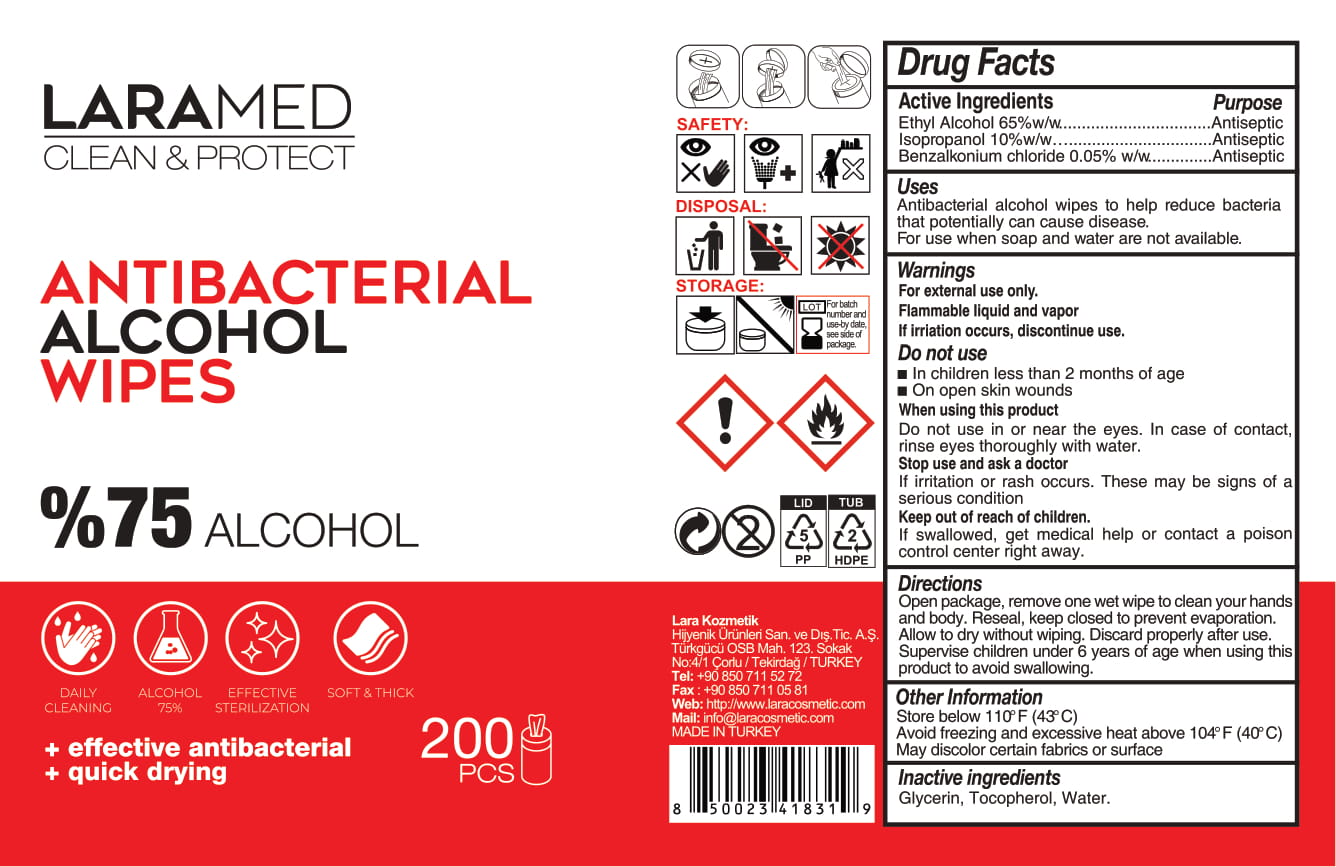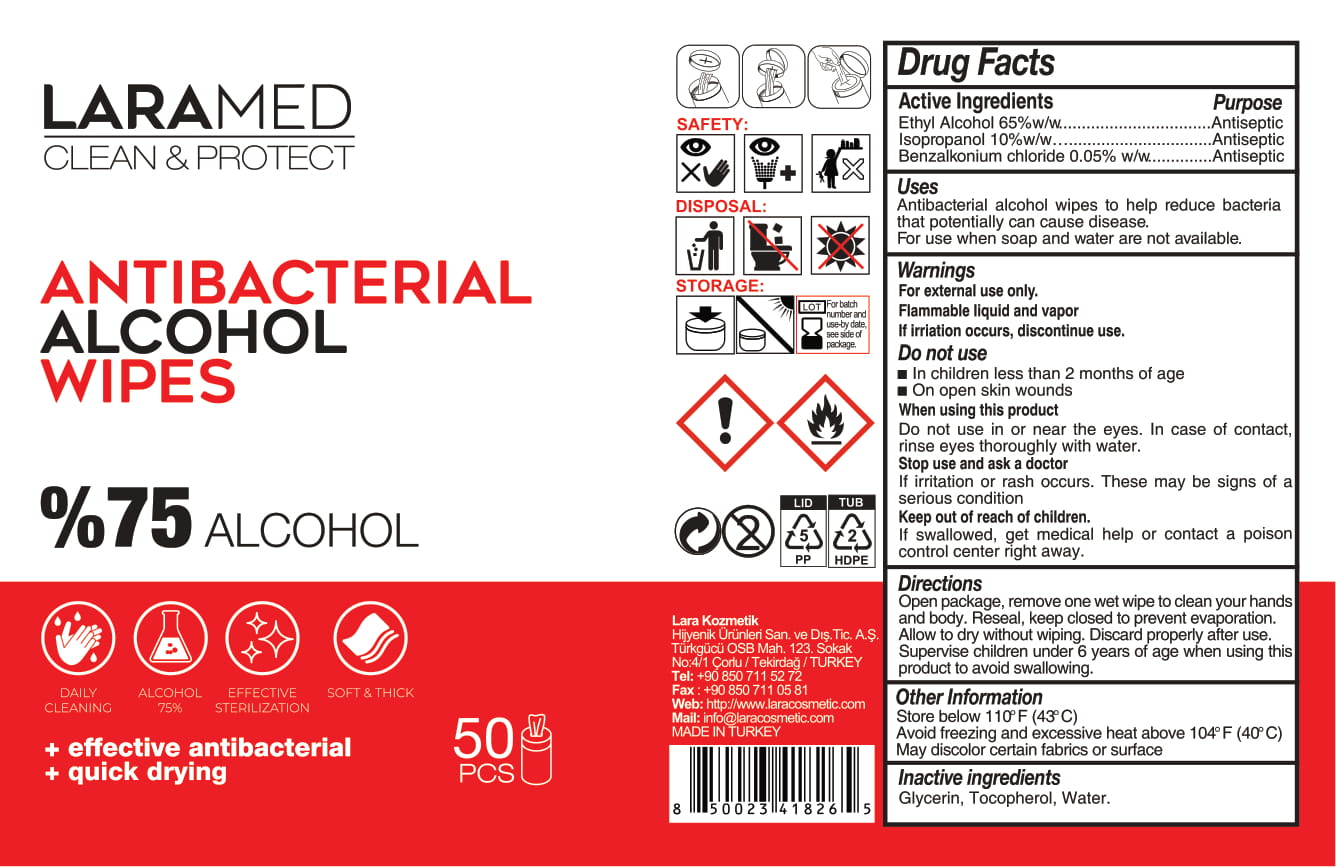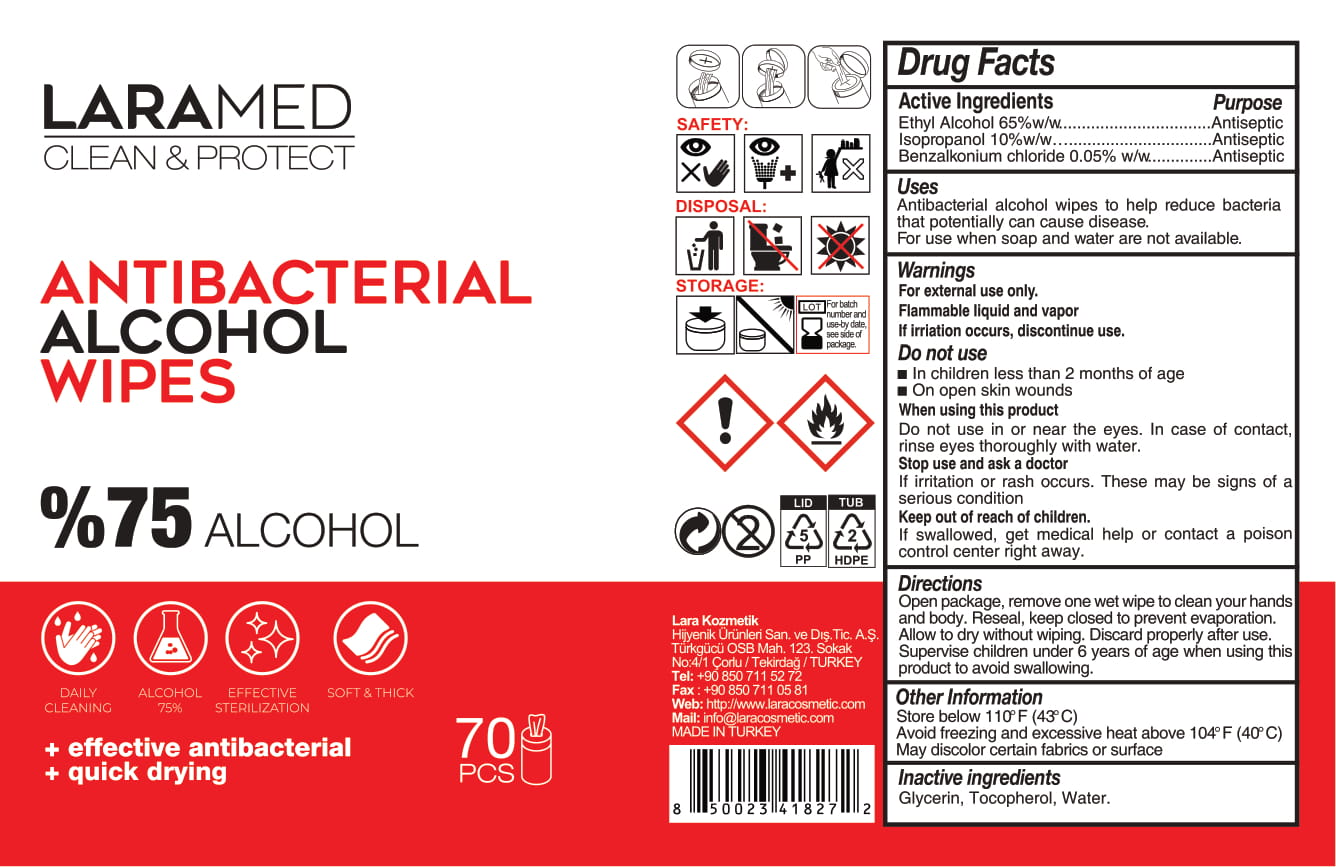 DRUG LABEL: LARAMED Antibacterial Alcohol Wipes
NDC: 86994-007 | Form: CLOTH
Manufacturer: LARA KOZMETIK HIJYENIK URUNLERI SANAYI VE DIS TICARET ANONIM SIRKETI
Category: otc | Type: HUMAN OTC DRUG LABEL
Date: 20201011

ACTIVE INGREDIENTS: ALCOHOL 65 g/100 g; ISOPROPYL ALCOHOL 10 g/100 g; BENZALKONIUM CHLORIDE 0.05 g/100 g
INACTIVE INGREDIENTS: GLYCERIN; TOCOPHEROL; WATER

LARAMED ANTIBACTERIAL ALCOHOL WIPES

This is a hand sanitizer manufactured according to the Temporary Policy for Preparation of Certain Alcohol-Based Hand Sanitizer Products During the Public Health Emergency (CoViD-19); Guidance for Industry.

The hand sanitizer is manufactured using only the following United States Pharmacopoeia (USP) grade ingredients in the preparation of the product (percentage in final product formulation) consistent with World Health Organization (WHO) recommendations:

1. Alcohol (ethanol) (USP or Food Chemical Codex (FCC) grade) (65%, weight/weight (w/w)) in an aqueous solution denatured according to Alcohol and Tobacco Tax and Trade Bureau regulations in 27 CFR part 20.
2. Isopropanol 10%, (w/w)
3. Benzalkonium Chloride 0.05%, (w/w)
4. Glycerol
5. Tocopherol
6. Sterile distilled water or boiled cold water.

The firm does not add other active or inactive ingredients. Different or additional ingredients may impact the quality and potency of the product.

Active Ingredient(s)

Alcohol 65% w/w. Purpose: Antiseptic

Isopropanol 10% w/w. Purpose: Antiseptic

Benzalkonium chloride 0.05% w/w. Purpose: Antiseptic

Purpose

Antiseptic, Hand Sanitizer

Use

Hand Sanitizer to help reduce bacteria that potentially can cause disease. For use when soap and water are not available.

Warnings

For external use only. Flammable liquid and vapor.

Do not use

- in children less than 2 months of age
- on open skin wounds

When using this product do not use in or near eyes. In case of contact with eyes, rinse eyes thoroughly with water.
Stop use and ask a doctor if irritation or rash occurs. These may be signs of a serious condition.
Keep out of reach of children. If swallowed, get medical help or contact a Poison Control Center right away.

Stop use and ask a doctor if irritation or rash occurs. These may be signs of a serious condition.

Keep out of reach of children. If swallowed, get medical help or contact a Poison Control Center right away.

Directions

- Open package, removeonewetwipetocleanyourhands| and body. Reseal, keep closed to prevent evaporation. Allow to dry without wiping. Discard properly after use.
- Supervise children under 6 years of age when using this product to avoid swallowing.

Other information

- Store below 110F (43 C)
- Avoid freezing and excessive heat above 40C (104F)
- May discolor certain fabrics or surface.

Inactive ingredients

Glycerol
Tocopherol

purified water USP